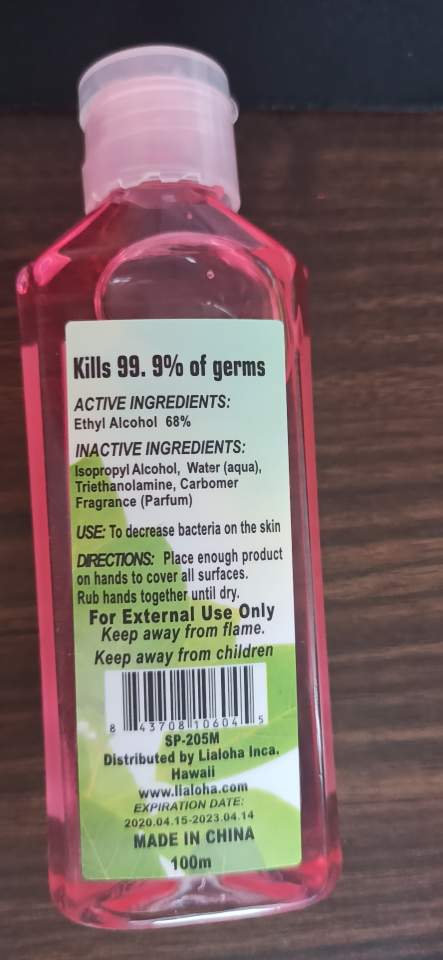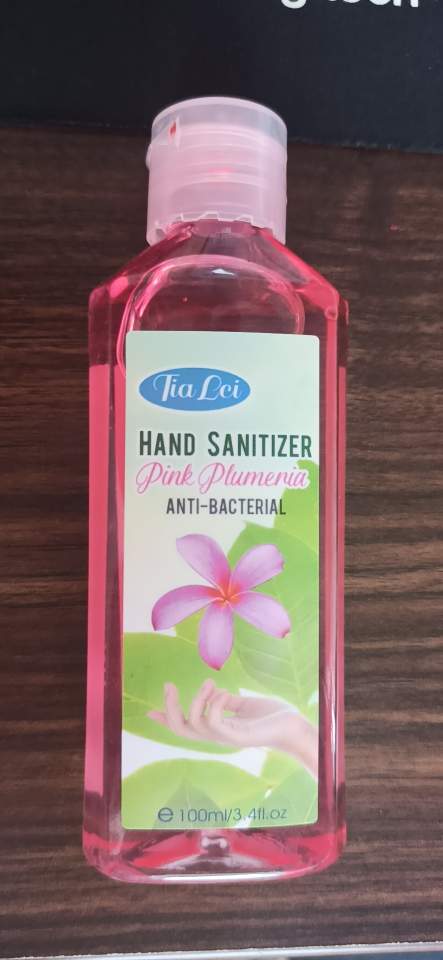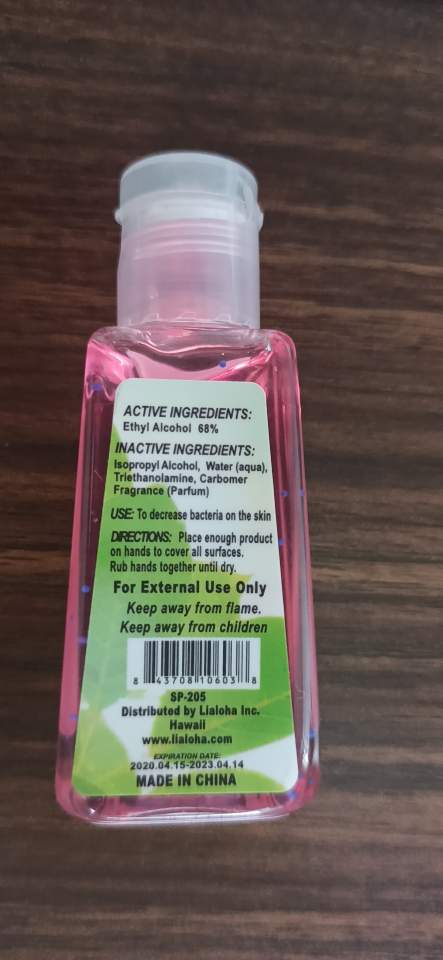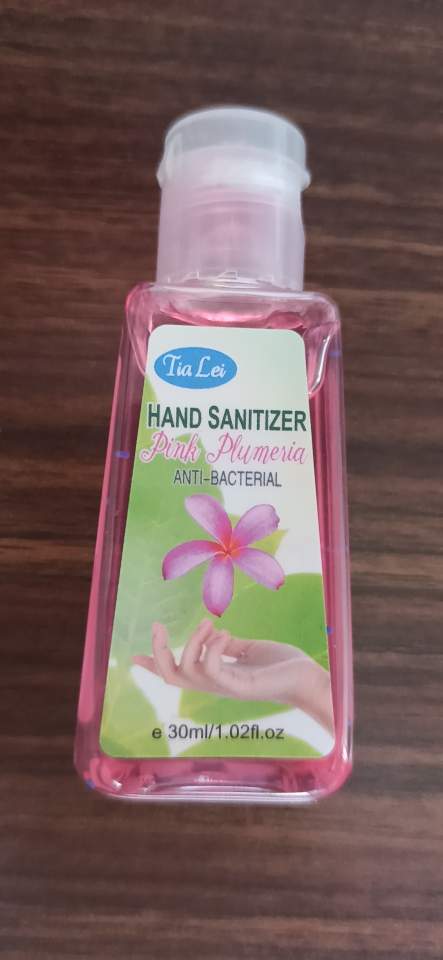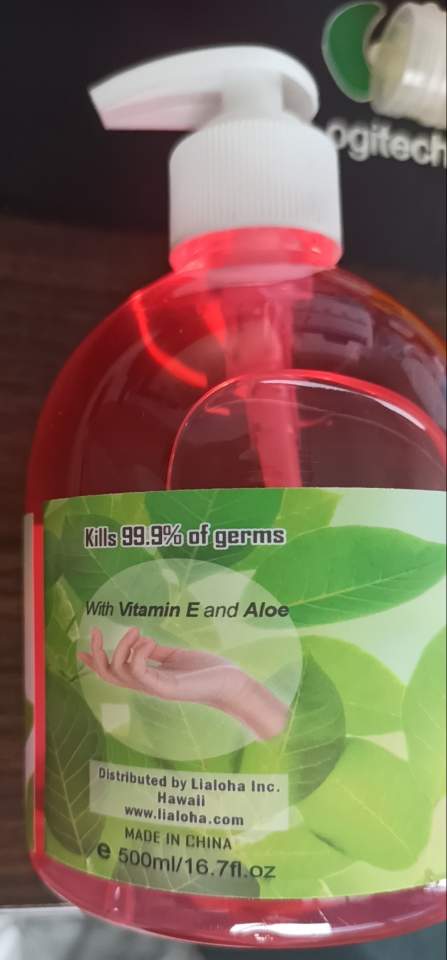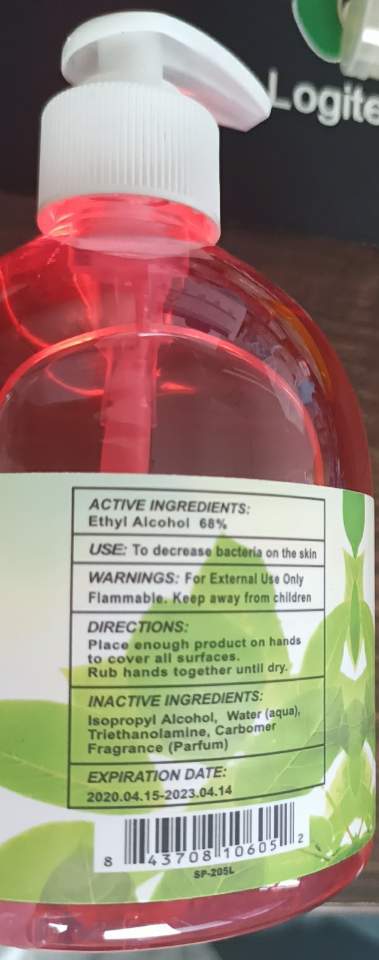 DRUG LABEL: Hand Sanitizer Pink Plumeria
NDC: 54225-004 | Form: GEL
Manufacturer: Yiwu Sloggi Cosmetics Co.,ltd
Category: otc | Type: HUMAN OTC DRUG LABEL
Date: 20211209

ACTIVE INGREDIENTS: ALCOHOL 68 mL/68 mL
INACTIVE INGREDIENTS: CARBOMER 940; ISOPROPYL ALCOHOL; WATER

Active Ingredient(s): Ethyl Alcohol 68%

Purpose: Antiseptic

INACTIVE INGREDIENT

Isopropyl Alcohol

Water

Triethanolamine

Carbomer

Fragrance

INDICATIONS AND USAGE

Rub hands together until dry.

Keep away from children.

PACKAGE LABEL

30mL Pink Plumeria NDC 54225-004-01

100mL Pink Plumeria NDC 54225-004-02

500mL Pink Plumeria NDC 54225-004-03